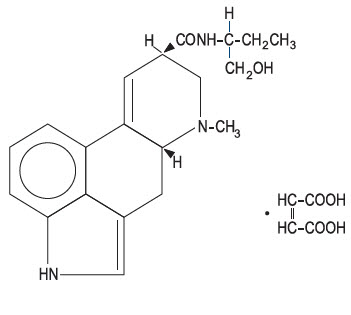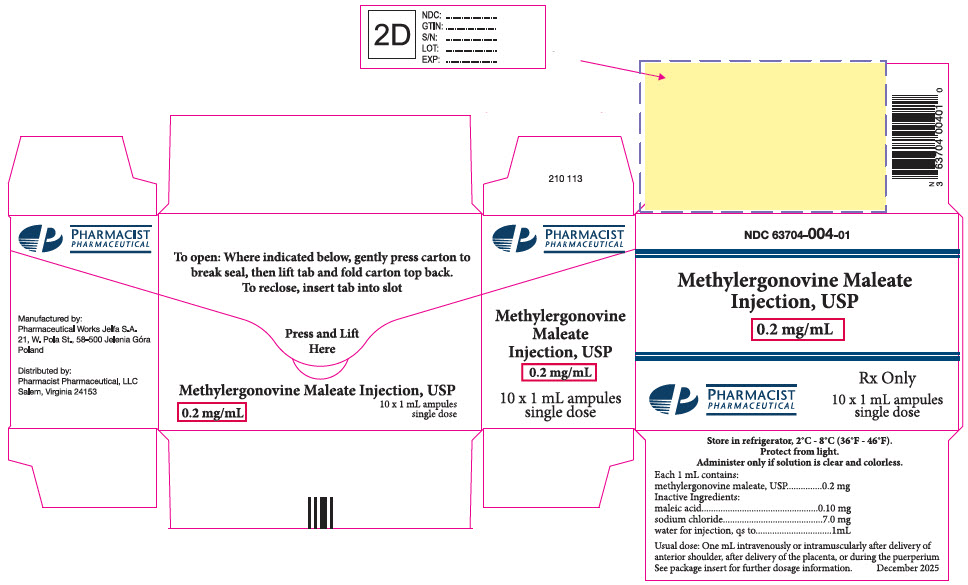 DRUG LABEL: METHYLERGONOVINE MALEATE
NDC: 63704-004 | Form: INJECTION, SOLUTION
Manufacturer: Pharmacist Pharmaceutical, LLC
Category: prescription | Type: HUMAN PRESCRIPTION DRUG LABEL
Date: 20251212

ACTIVE INGREDIENTS: methylergonovine maleate 0.2 mg/1 mL
INACTIVE INGREDIENTS: maleic acid 0.1 mg/1 mL; sodium chloride 7 mg/1 mL; water

Methylergonovine Maleate
Injection, USP

Rx only

DESCRIPTION

Methylergonovine Maleate Injection, USP is a semi-synthetic ergot alkaloid used for the prevention and control of postpartum hemorrhage.

Methylergonovine Maleate Injection, USP is available in sterile ampules of 1 mL, containing 0.2 mg methylergonovine maleate for intramuscular or intravenous injection.

Ampules: 1 mL, clear, colorless solution.
Active Ingredient: methylergonovine maleate, USP, 0.2 mg.
Inactive Ingredients: maleic acid, 0.10 mg; sodium chloride, 7.0 mg; water for injection, qs to 1 mL.

Chemically, methylergonovine maleate is designated as ergoline-8-carboxamide, 9,10-didehydro-N-[l-(hydroxymethyl)propyl]-6-methyl-, [8β(S)]-, (Z)-2-butenedioate (1:1) (salt). Its structural formula is

C20H25N3O2∙C4H4O4 Mol. wt. - 455.51

CLINICAL PHARMACOLOGY

Mechanism of Action

Methylergonovine maleate acts directly on the smooth muscle of the uterus and increases the tone, rate, and amplitude of rhythmic contractions. Thus, it induces a rapid and sustained tetanic uterotonic effect which shortens the third stage of labor and reduces blood loss.

Pharmacodynamics

The onset of action after IV administration is immediate; after I.M. administration, 2-5 minutes, and after oral administration, 5-10 minutes.

Pharmacokinetics

Pharmacokinetic studies following an IV injection have shown that methylergonovine is rapidly distributed from plasma to peripheral tissues within 2-3 minutes or less. The bioavailability after oral administration was reported to be about 60% with no accumulation after repeated doses. During delivery, with intramuscular injection, bioavailability increased to 78%. Ergot alkaloids are mostly eliminated by hepatic metabolism and excretion, and the decrease in bioavailability following oral administration is probably a result of first-pass metabolism in the liver.

Bioavailability studies conducted in fasting healthy female volunteers have shown that oral absorption of a 0.2 mg methylergonovine tablet was fairly rapid with a mean peak plasma concentration of 3243 ± 1308 pg/mL observed at 1.12 ± 0.82 hours. A delayed gastrointestinal absorption (Tmax about 3 hours) of methylergonovine maleate tablet might be observed in postpartum women during continuous treatment with this oxytocic agent.

For a 0.2 mg intramuscular (IM) injection, a mean peak plasma concentration of 5918 ± 1952 pg/mL was observed at 0.41 ± 0.21 hours. The extent of absorption of the tablet, based upon methylergonovine plasma concentrations, was found to be equivalent to that of the IM solution given orally, and the extent of oral absorption of the IM solution was proportional to the dose following administration of 0.1, 0.2, and 0.4 mg. When given intramuscularly, the extent of absorption of methylergonovine maleate solution was about 25% greater than the tablet. The volume of distribution (Vdss/F) of intramuscularly administered methylergonovine was calculated to be 56.1 ± 17.0 liters, and the plasma clearance (CLp/F) was calculated to be 14.4 ± 4.5 liters per hour. The decline of plasma level of intramuscularly administered methylergonovine was biphasic with a mean elimination half-life of 3.39 hours (range 1.5 to 12.7 hours).

INDICATIONS AND USAGE

Following delivery of the placenta, for routine management of uterine atony, hemorrhage and subinvolution of the uterus. For control of uterine hemorrhage in the second stage of labor following delivery of the anterior shoulder.

CONTRAINDICATIONS

Hypertension; toxemia; pregnancy; and hypersensitivity.

WARNINGS

General

This drug should not be administered I.V. routinely because of the possibility of inducing sudden hypertensive and cerebrovascular accidents. If I.V. administration is considered essential as a lifesaving measure, methylergonovine maleate should be given slowly over a period of no less than 60 seconds with careful monitoring of blood pressure. Intra-arterial or periarterial injection should be strictly avoided.

Caution should be exercised in the presence of impaired hepatic or renal function.

Coronary artery disease

Patients with coronary artery disease or risk factors for coronary artery disease (e.g., smoking, obesity, diabetes, high cholesterol) may be more susceptible to developing myocardial ischemia and infarction associated with methylergonovine-induced vasospasm.

Risk of Adverse Reactions or Reduced Therapeutic Effect Due to Drug Interactions

The concomitant use of Methylergonovine Maleate and certain drugs may result in potentially significant drug interactions, some of which may lead to adverse reactions or reduced therapeutic effect of Methylergonovine Maleate or the concomitant drug. (see CONTRAINDICATION and DRUG INTERACTION)

Medication errors

Inadvertent administration of Methylergonovine Maleate Injection to newborn infants has been reported. In these cases of inadvertent neonatal exposure, symptoms such as respiratory depression, convulsions, cyanosis and oliguria have been reported. Usual treatment is symptomatic. However, in severe cases, respiratory and cardiovascular support is required.

Methylergonovine Maleate Injection has been administered instead of vitamin K and Hepatitis B vaccine, medications which are routinely administered to the newborn. Due to the potential for accidental neonatal exposure, Methylergonovine Maleate Injection should be stored separately from medications intended for neonatal administration.

PRECAUTIONS

General

Caution should be exercised in the presence of sepsis, obliterative vascular disease. Also use with caution during the second stage of labor. The necessity for manual removal of a retained placenta should occur only rarely with proper technique and adequate allowance of time for its spontaneous separation.

Drug Interactions

CYP 3A4 Inhibitors (e.g., Macrolide Antibiotics and Protease Inhibitors)

There have been rare reports of serious adverse events in connection with the coadministration of certain ergot alkaloid drugs (e.g., dihydroergotamine and ergotamine) and potent CYP 3A4 inhibitors, resulting in vasospasm leading to cerebral ischemia and/or ischemia of the extremities. Although there have been no reports of such interactions with methylergonovine alone, strong and moderate CYP 3A4 inhibitors should not be co-administered with methylergonovine. Examples of some of the strong CYP 3A4 inhibitors include saquinavir, grapefruit juice, nefazodone, macrolide antibiotics (e.g., troleandomycin, clarithromycin), HIV protease or reverse transcriptase inhibitors (e.g., ritonavir, indinavir, nelfinavir) or azole antifungals (e.g., ketoconazole, itraconazole, voriconazole). Moderate inhibitors include fluconazole, fluvoxamine and clotrimazole. Weak CYP 3A4 inhibitors should be administered with caution. Weak inhibitors include chlorzoxazone, cilostazol, and ranitidine. These lists are not exhaustive, and the prescriber should consider the effects on CYP 3A4 of other agents being considered for concomitant use with methylergonovine.

CYP3A4 inducers

Drugs (e.g. nevirapine, rifampin) that are strong inducers of CYP3A4 are likely to decrease the pharmacological action of Methylergonovine Maleate Injection.

Beta-blockers

Caution should be exercised when Methylergonovine Maleate Injection is used concurrently with beta-blockers. Concomitant administration with beta-blockers may enhance the vasoconstrictive action of ergot alkaloids.

Anesthetics

Anesthetics like halothane and methoxyflurane may reduce the oxytocic potency of Methylergonovine Maleate Injection.

Glyceryl trinitrate and other antianginal drugs

Methylergonovine maleate produces vasoconstriction and can be expected to reduce the effect of glyceryl trinitrate and other antianginal drugs.

No pharmacokinetic interactions involving other cytochrome P450 isoenzymes are known.

Caution should be exercised when Methylergonovine Maleate Injection is used concurrently with other vasoconstrictors, ergot alkaloids, or prostaglandins.

Carcinogenesis, Mutagenesis, Impairment of Fertility

No long-term studies have been performed in animals to evaluate carcinogenic potential. The effect of the drug on mutagenesis or fertility has not been determined.

Pregnancy

Use of Methylergonovine Maleate is contraindicated during pregnancy because of its uterotonic effects. (See INDICATIONS AND USAGE)

Animal reproductive studies have not been conducted with Methylergonovine Maleate. It is not known whether Methylergonovine Maleate can cause fetal harm or can affect reproductive capacity.

Labor and Delivery

The uterotonic effect of methylergonovine maleate is utilized after delivery to assist involution and decrease hemorrhage, shortening the third stage of labor. Caution should be exercised during the second stage of labor. The necessity for manual removal of a retained placenta should occur only rarely with proper technique and adequate allowance of time for its spontaneous separation.

Nursing Mothers

Mothers should not breast-feed during treatment with Methylergonovine Maleate Injection and at least 12 hours after administration of the last dose. Milk secreted during this period should be discarded. Methylergonovine Maleate may produce adverse effects in the breast-feeding infant. Methylergonovine Maleate may also reduce the yield of breast milk.

Pediatric Use

Safety and effectiveness in pediatric patients have not been established.

Geriatric Use

Clinical studies of methylergonovine maleate did not include sufficient number of subjects aged 65 and over to determine whether they respond differently from younger subjects. Other reported clinical experience has not identified differences in response between the elderly and younger patients. In general dose selection for an elderly patient should be cautious, usually starting at the low end of the dosing range, reflecting the greater frequency of decreased hepatic, renal, or cardiac function, and of concomitant disease or other drug therapy.

Hepatic Impairment

No studies have been performed in subjects with hepatic impairment. Methylergometrine is mostly eliminated by hepatic metabolism and excretion. Use with caution in patients with hepatic impairment.

Renal Impairment

No studies have been performed in subjects with renal impairment. Renal excretion contributes to the elimination of methylergometrine and its metabolites. Use with caution in patients with renal impairment.

ADVERSE REACTIONS

Clinical trials experience

Common Adverse Reactions

The most common adverse reaction is hypertension associated in several cases with seizure and/or headache. Hypotension has also been reported. Abdominal pain (caused by uterine contractions), nausea and vomiting have occurred occasionally.

Rare Adverse Reactions

Rarely observed reactions have included: acute myocardial infarction, transient chest pains, vasoconstriction, vasospasm, coronary arterial spasm, bradycardia, tachycardia, dyspnea, hematuria, thrombophlebitis, water intoxication, hallucinations, leg cramps, dizziness, tinnitus, nasal congestion, diarrhea, diaphoresis, palpitation, rash, and foul taste.

There have been rare isolated reports of anaphylaxis, without a proven causal relationship to the drug product.

Post marketing Experience

The following adverse drug reactions have been derived from post-marketing experience with Methylergonovine Maleate Injection via spontaneous case reports. Because these reactions are reported voluntarily from a population of uncertain size, it is not possible to reliably estimate their frequency which is therefore categorized as not known.

Nervous system disorders

Cerebrovascular accident, paraesthesia

Cardiac disorders

Ventricular fibrillation, ventricular tachycardia, angina pectoris, atrioventricular block

DRUG ABUSE AND DEPENDENCE

Methylergonovine maleate has not been associated with drug abuse or dependence of either a physical or psychological nature.

OVERDOSAGE

Symptoms of acute overdose may include: nausea, vomiting, oliguria, abdominal pain, numbness, tingling of the extremities, rise in blood pressure, in severe cases followed by hypotension, respiratory depression, hypothermia, convulsions, and coma.

Because reports of overdosage with methylergonovine maleate are infrequent, the lethal dose in humans has not been established. The oral LD50 (in mg/kg) for the mouse is 187, the rat 93, and the rabbit 4.5. Several cases of accidental Methylergonovine Maleate Injection in newborn infants have been reported, and in such cases 0.2 mg represents an overdose of great magnitude. However, recovery occurred in all but one case following a period of respiratory depression, hypothermia, hypertonicity with jerking movements, and convulsions.

Also, several children 1-3 years of age have accidentally ingested up to 10 tablets (2 mg) with no apparent ill effects. A postpartum patient took 4 tablets at one time in error and reported paresthesias and clamminess as her only symptoms.

Treatment of acute overdosage is symptomatic and includes the usual procedures of:

1. removal of offending drug by inducing emesis, gastric lavage, catharsis, and supportive diuresis.
2. maintenance of adequate pulmonary ventilation, especially if convulsions or coma develop.
3. correction of hypotension with pressor drugs as needed.
4. control of convulsions with standard anticonvulsant agents.
5. control of peripheral vasospasm with warmth to the extremities if needed.

DOSAGE AND ADMINISTRATION

Parenteral drug products should be inspected visually for particulate matter and discoloration prior to administration.

Intramuscularly

1 mL, 0.2 mg, after delivery of the anterior shoulder, after delivery of the placenta, or during the puerperium. May be repeated as required, at intervals of 2-4 hours.

Intravenously

1 mL, 0.2 mg, administered slowly over a period of no less than 60 seconds (See WARNINGS).

HOW SUPPLIED

Ampules

1 mL size

Boxes of 10 | NDC 63704-004-01

Store and Dispense

Ampules

Store in refrigerator, 2°C-8°C (36°F-46°F). Protect from light. Administer only if solution is clear and colorless.

REV: June 2025

Manufactured by:
Pharmaceutical Works Jelfa S.A. 58-500 Jelenia Góra, Poland

Distributed by:
Pharmacist Pharmaceutical, LLC
Salem, Virginia 24153

210114

PRINCIPAL DISPLAY PANEL - 1 mL Ampule Box

NDC 63704-004-01

Methylergonovine Maleate
Injection, USP

0.2 mg/mL

Rx Only

PHARMACIST
PHARMACEUTICAL

10 x 1 mL ampules
single dose